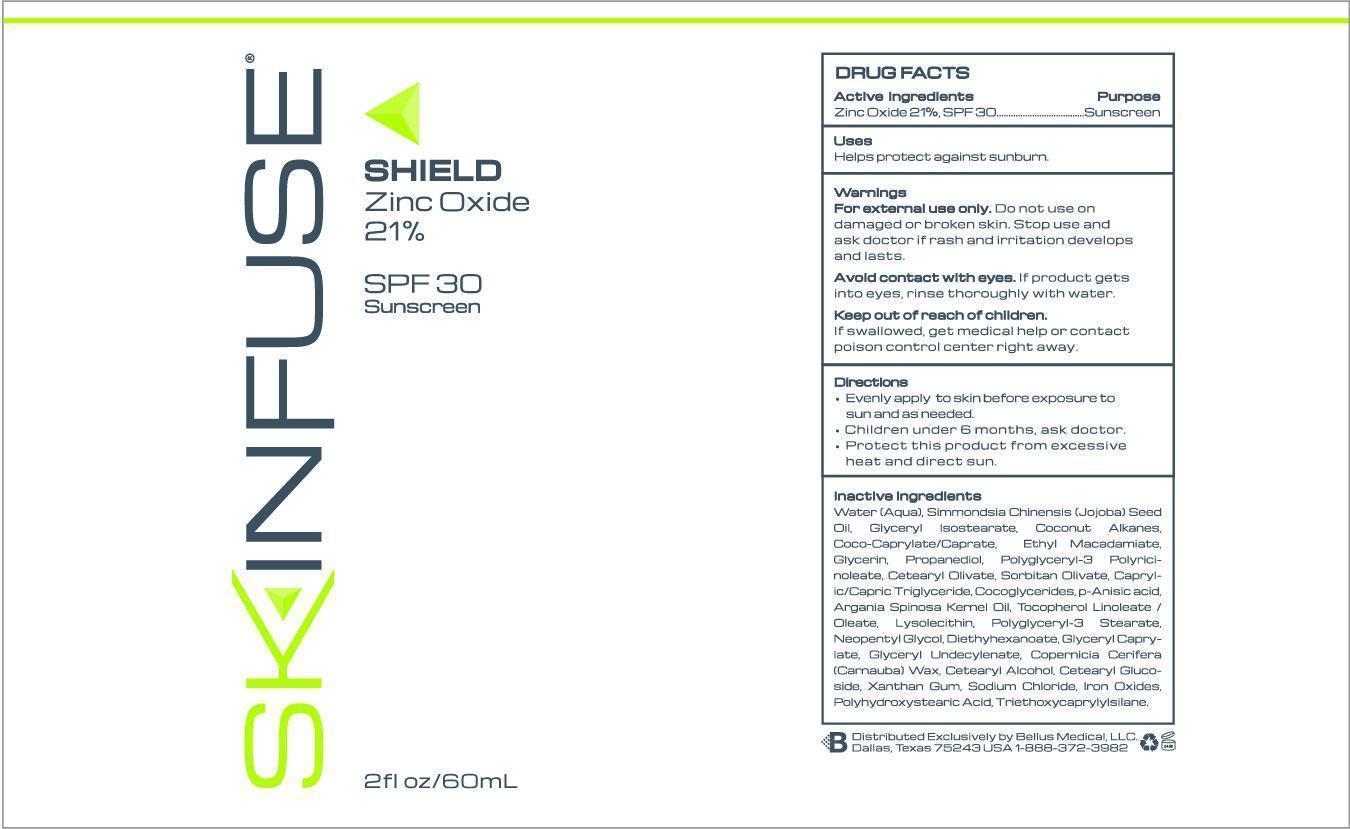 DRUG LABEL: Skinfuse Shield
NDC: 59958-240 | Form: CREAM
Manufacturer: Owen Biosciences, Inc.
Category: otc | Type: HUMAN OTC DRUG LABEL
Date: 20250110

ACTIVE INGREDIENTS: ZINC OXIDE 21 g/100 g
INACTIVE INGREDIENTS: WATER 34 g/100 g; GLYCERIN 5 g/100 g; PROPANEDIOL 5 g/100 g; POLYGLYCERYL-3 RICINOLEATE 4 g/100 g; JOJOBA OIL 8.97 g/100 g; ETHYL MACADAMIATE 5 g/100 g

Skinfuse Shield 60g

Active Ingredients

Zinc Oxide 21%

Purpose

Sunscreen

Warnings

For external use only.

Avoid Contact with eyes.

Keep out of reach of children

Directions

Evenly apply to skin before exposure to sun as needed.